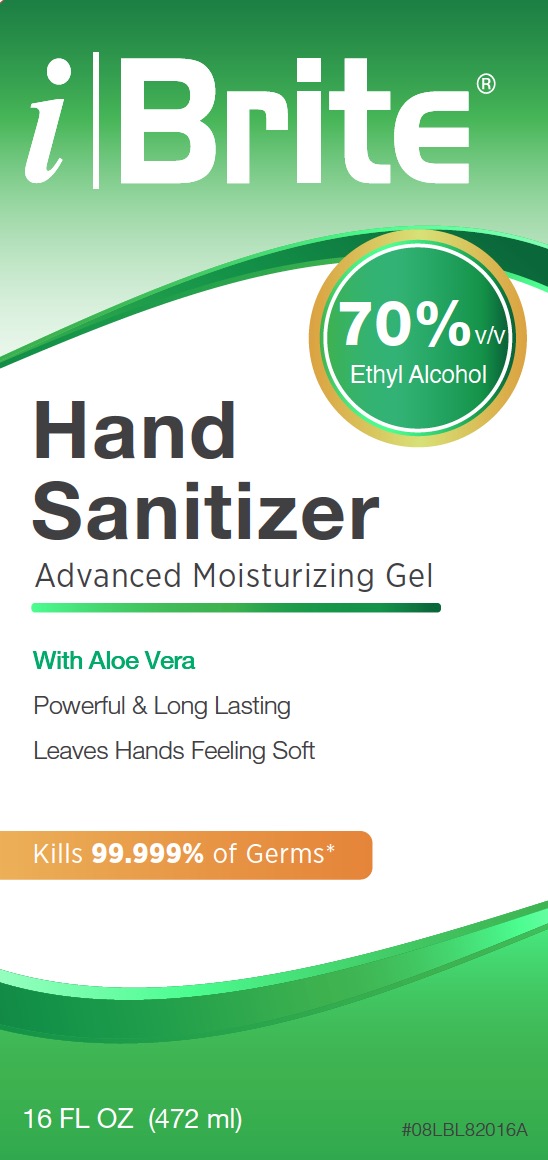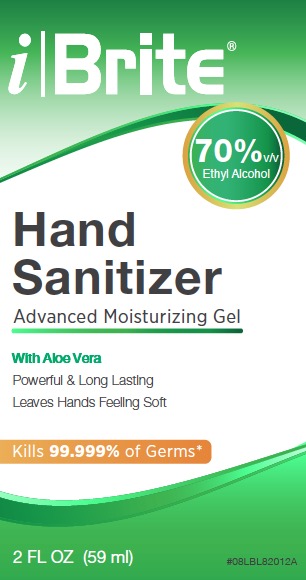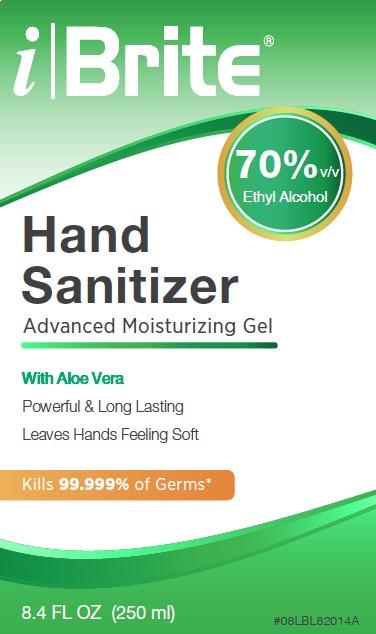 DRUG LABEL: iBrite Hand Sanitizer
NDC: 10129-080 | Form: GEL
Manufacturer: Gingi-Pak
Category: otc | Type: HUMAN OTC DRUG LABEL
Date: 20200410

ACTIVE INGREDIENTS: ALCOHOL 70 mL/100 mL
INACTIVE INGREDIENTS: SULISOBENZONE 0.05 g/100 mL; CARBOMER HOMOPOLYMER TYPE C (ALLYL PENTAERYTHRITOL CROSSLINKED) 0.32 g/100 mL; GLYCERIN 0.5 mL/100 mL; ALOE VERA LEAF 0.5 mL/100 mL; WATER 29 mL/100 mL; AMINOMETHYLPROPANOL 0.16 g/100 mL

iBrite Hand Sanitizer

Active Ingredient(s)

Ethyl Alcohol 70% v/v. Purpose: Antiseptic

Purpose

Antiseptic

Use

Reduce bacteria that potentially can cause disease.

Recommened for repeated use

Warnings

For external use only. Flammable. Keep away from heat or flame

Do not use

Do not apply around eyes.

When using this product

- keep out of eyes. In case of contact with eyes, flush thoroughly with water.
- Avoid contact with broken skin.
- Do not inhale or ingest.

Stop use and ask a doctor if

irritation or rash occurs. These may be signs of a serious condition.

Keep out of reach of children.

If swallowed, get medical help or contact a Poison Control Center right away.

Directions

- Dispense enough gel in your palm to cover all surfaces of hands and finger. Rub hands together vigorously until dry.
- Usage on children requires adult supervision, not recommended for infants.
- Work best on clean and dry hands.

Other information

- Store below 43 C (110F)
- May discolor certain fabrics or surfaces

Inactive ingredients

Distilled Water, Glycerin, Carbomer 940, Benzophenone-4, Aloe Vera, Aminomethyl Propanol.